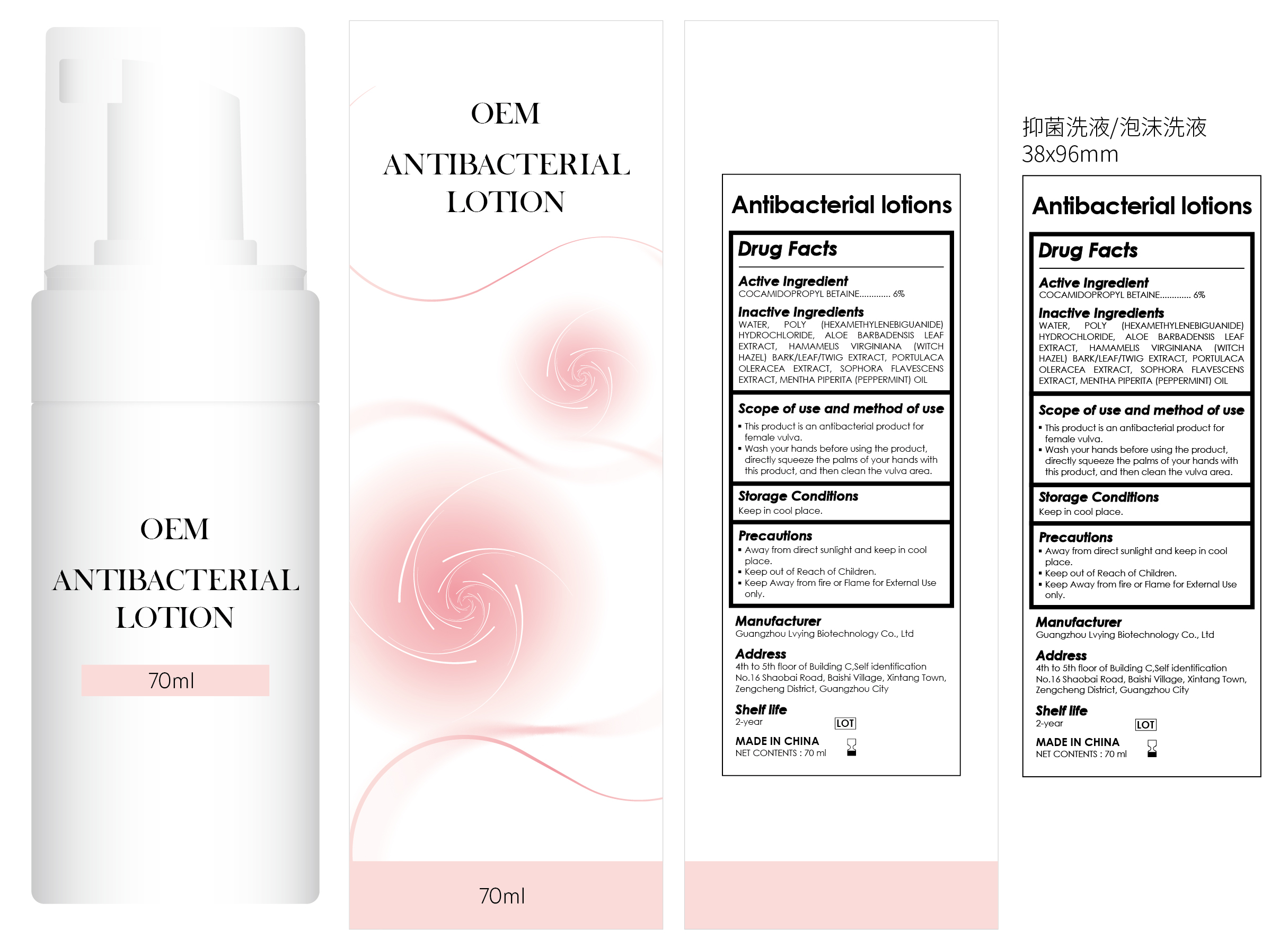 DRUG LABEL: Antibacterial lotions
NDC: 84260-001 | Form: LIQUID
Manufacturer: Guangzhou Lvying Biotechnology Co., Ltd
Category: otc | Type: HUMAN OTC DRUG LABEL
Date: 20240516

ACTIVE INGREDIENTS: COCAMIDOPROPYL BETAINE 6 g/100 mL
INACTIVE INGREDIENTS: HAMAMELIS VIRGINIANA ROOT BARK/STEM BARK; PORTULACA OLERACEA WHOLE; MENTHA PIPERITA; SOPHORA FLAVESCENS WHOLE; POLIHEXANIDE HYDROCHLORIDE; ALOE VERA LEAF; WATER

Antibacterial lotions

ACTIVE INGREDIENT

poly (hexamethylenebiguanide) hydrochloride 0.2%

PURPOSE

This product is an antibacterial product forfemale vulva.

KEEP OUT OF REACH OF CHILDREN SECTION

INDICATIONS AND USAGE

This product is an antibacterial product forfemale vulva.
Wash your hands before using the productdirectly squeeze the palms of your hands withthis product, and then clean the vulva area.

WARNINGS

For external use only

DOSAGE AND ADMINISTRATION

This product is an antibacterial product forfemale vulva.
Wash your hands before using the productdirectly squeeze the palms of your hands withthis product, and then clean the vulva area.

STORAGE AND HANDLING

Away from direct sunlight and keep in coolplace.

Keep out of Reach of Children.

Keep Away form fire or Flame for External Use omly.

INACTIVE INGREDIENT

WATER,HAMAMELIS VIRGINIANA ROOT BARK/STEM BARK,PORTULACA OLERACEA WHOLE,MENTHA PIPERITA,ALOE VERA LEAF,COCAMIDOPROPYL BETAINE,SOPHORA FLAVESCENS WHOLE